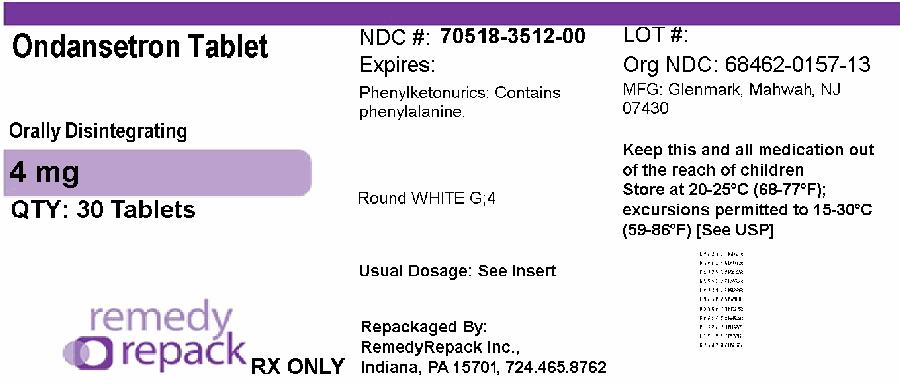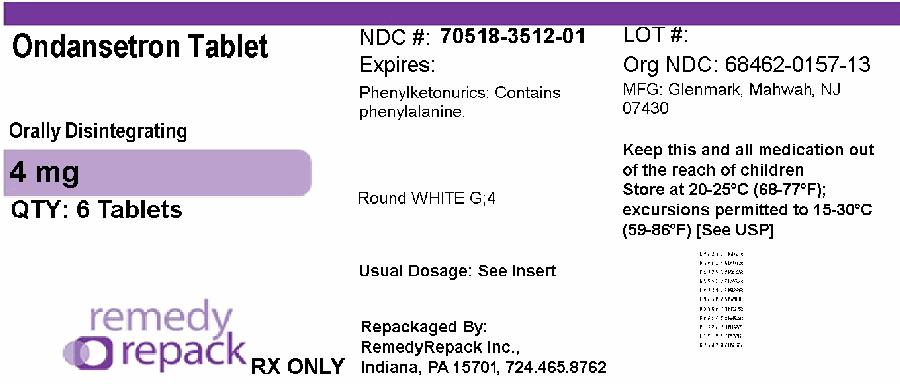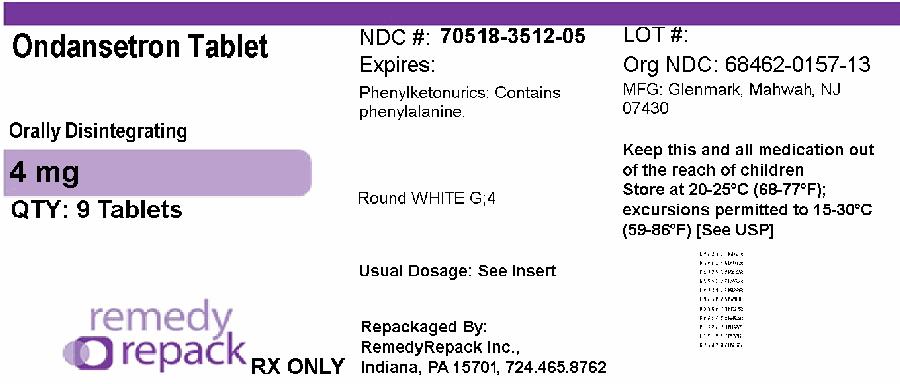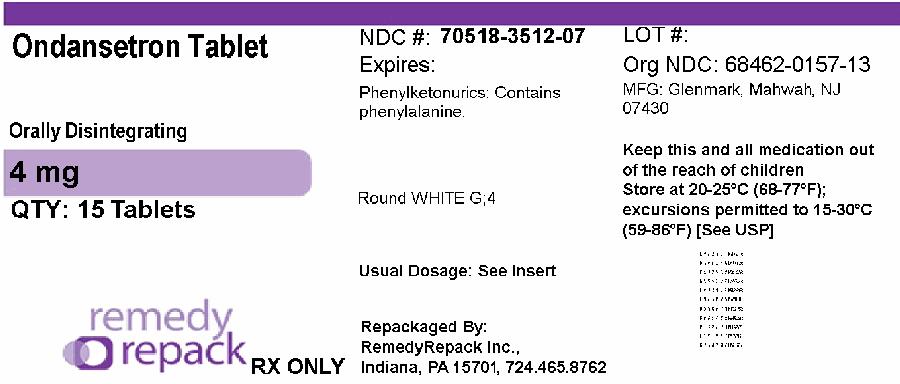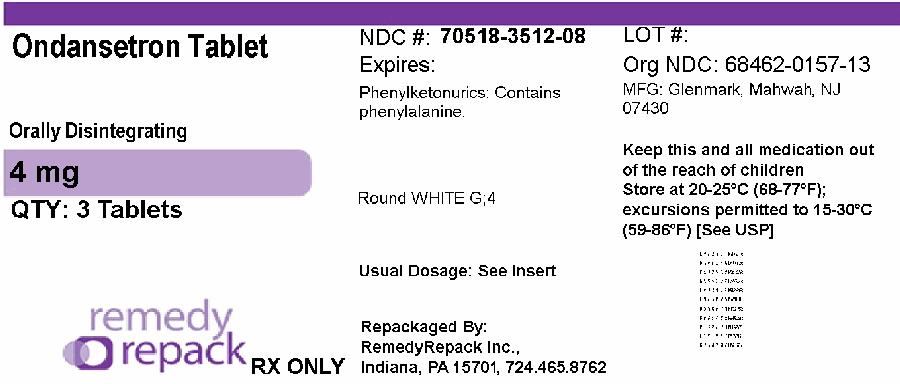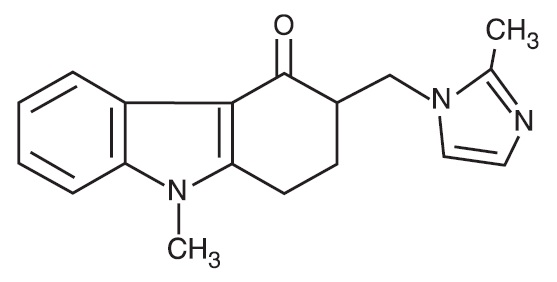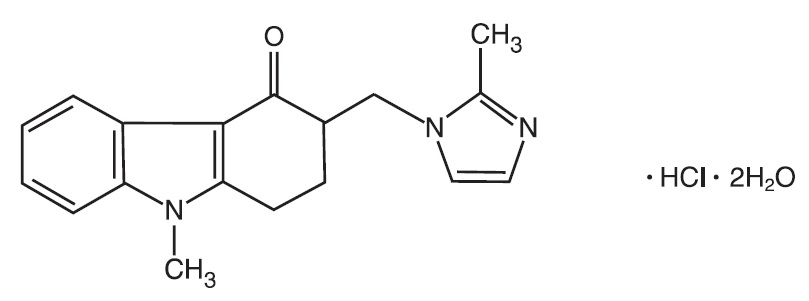 DRUG LABEL: Ondansetron
NDC: 70518-3512 | Form: TABLET, ORALLY DISINTEGRATING
Manufacturer: REMEDYREPACK INC.
Category: prescription | Type: HUMAN PRESCRIPTION DRUG LABEL
Date: 20260302

ACTIVE INGREDIENTS: ONDANSETRON 4 mg/1 1
INACTIVE INGREDIENTS: ASPARTAME; SILICON DIOXIDE; CROSPOVIDONE (120 .MU.M); MAGNESIUM STEARATE; MANNITOL; SODIUM STEARYL FUMARATE

HIGHLIGHTS OF PRESCRIBING INFORMATION

These highlights do not include all the information needed to use ONDANSETRON TABLETS and ONDANSETRON ORALLY DISINTEGRATING TABLETS safely and effectively. See full prescribing information for ONDANSETRON TABLETS and ONDANSETRON ORALLY DISINTEGRATING TABLETS.
Initial U.S. Approval: 1991

6. Adverse Reactions

The most common adverse reactions in adults for the:

prevention of chemotherapy-induced (≥5%) are: headache, malaise/fatigue, constipation, diarrhea. (6.1)
prevention of radiation-induced nausea and vomiting (≥2%) are: headache, constipation, and diarrhea. (6.1)
prevention of postoperative nausea and vomiting (≥9%) are: headache and hypoxia. (6.1)

To report SUSPECTED ADVERSE REACTIONS, contact Glenmark Pharmaceuticals Inc., USA at 1 (888) 721-7115 or FDA at 1-800-FDA-1088 or www.fda.gov/medwatch.

FULL PRESCRIBING INFORMATION

7 DRUG INTERACTIONS

7.1 Serotonergic Drugs

Serotonin syndrome (including altered mental status, autonomic instability, and neuromuscular symptoms) has been described following the concomitant use of 5-HT3 receptor antagonists and other serotonergic drugs, including SSRIs and SNRIs. Monitor for the emergence of serotonin syndrome. If symptoms occur, discontinue ondansetron and initiate supportive treatment [see Warnings and Precautions (5.3)] .

7.2 Drugs Affecting Cytochrome P-450 Enzymes

Ondansetron does not itself appear to induce or inhibit the cytochrome P‑450 drug‑metabolizing enzyme system of the liver [see Clinical Pharmacology (12.3)] . Because ondansetron is metabolized by hepatic cytochrome P‑450 drug‑metabolizing enzymes (CYP3A4, CYP2D6, CYP1A2), inducers or inhibitors of these enzymes may change the clearance and, hence, the half‑life of ondansetron. In patients treated with potent inducers of CYP3A4 (i.e., phenytoin, carbamazepine, and rifampin), the clearance of ondansetron was significantly increased and ondansetron blood concentrations were decreased. However, on the basis of available data, no dosage adjustment for ondansetron is recommended for patients on these drugs [see Clinical Pharmacology (12.3)] .

7.3 Tramadol

Although no pharmacokinetic drug interaction between ondansetron and tramadol has been observed, data from 2 small trials indicate that when used together, ondansetron may increase patient-controlled administration of tramadol. Monitor patients to ensure adequate pain control when ondansetron is administered with tramadol.

7.4 Chemotherapy

Carmustine, etoposide, and cisplatin do not affect the pharmacokinetics of ondansetron.

In a crossover trial in 76 pediatric patients, intravenous ondansetron did not increase systemic concentrations of high-dose methotrexate.

7.5 Alfentanil and Atracurium

Ondansetron does not alter the respiratory depressant effects produced by alfentanil or the degree of neuromuscular blockade produced by atracurium. Interactions with general or local anesthetics have not been studied.

8 USE IN SPECIFIC POPULATIONS

8.1 Pregnancy

Risk Summary

Published epidemiological studies on the association between ondansetron use and major birth defects have reported inconsistent findings and have important methodological limitations that preclude conclusions about the safety of ondansetron use in pregnancy (see Data). Available postmarketing data have not identified a drug-associated risk of miscarriage or adverse maternal outcomes. Reproductive studies in rats and rabbits did not show evidence of harm to the fetus when ondansetron was administered during organogenesis at approximately 6 and 24 times the maximum recommended human oral dose of 24 mg/day, based on body surface area (BSA), respectively (see Data).

The background risk of major birth defects and miscarriage for the indicated population is unknown. All pregnancies have a background risk of birth defect, miscarriages, or other adverse outcomes. In the US general population, the estimated background risk of major birth defects and miscarriages in clinically recognized pregnancies is 2% to 4% and 15% to 20%, respectively.

Data

Human Data

Available data on ondansetron use in pregnant women from several published epidemiological studies preclude an assessment of a drug-associated risk of adverse fetal outcomes due to important methodological limitations, including the uncertainty of whether women who filled a prescription actually took the medication, the concomitant use of other medications or treatments, recall bias, and other unadjusted confounders.

Ondansetron exposure in utero has not been associated with overall major congenital malformations in aggregate analyses. One large retrospective cohort study examined 1970 women who received a prescription for ondansetron during pregnancy and reported no association between ondansetron exposure and major congenital malformations, miscarriage, stillbirth, preterm delivery, infants of low birth weight, or infants small for gestational age.

Two large retrospective cohort studies and one case-control study have assessed ondansetron exposure in the first trimester and risk of cardiovascular defects with inconsistent findings. Relative risks (RR) ranged from 0.97 (95% CI 0.86 to 1.10) to 1.62 (95% CI 1.04, 2.54). A subset analysis in one of the cohort studies observed that ondansetron was specifically associated with cardiac septal defects (RR 2.05, 95% CI 1.19, 3.28); however, this association was not confirmed in other studies.

Several studies have assessed ondansetron and the risk of oral clefts with inconsistent findings. A retrospective cohort study of 1.8 million pregnancies in the US Medicaid Database showed an increased risk of oral clefts among 88,467 pregnancies in which oral ondansetron was prescribed in the first trimester (RR 1.24, 95% CI 1.03, 1.48), but no such association was reported with intravenous ondansetron in 23,866 pregnancies (RR 0.95, 95% CI 0.63, 1.43). In the subgroup of women who received both forms of administration, the RR was 1.07 (95% CI 0.59, 1.93). Two case-control studies, using data from birth defects surveillance programs, reported conflicting associations between maternal use of ondansetron and isolated cleft palate (OR 1.6 [95% CI 1.1, 2.3] and 0.5 [95% CI 0.3, 1.0]). It is unknown whether ondansetron exposure in utero in the cases of cleft palate occurred during the time of palate formation (the palate is formed between the 6th and 9th weeks of pregnancy).

Animal Data

In embryo-fetal development studies in rats and rabbits, pregnant animals received oral doses of ondansetron up to 15 mg/kg/day and 30 mg/kg/day, respectively, during the period of organogenesis. With the exception of a slight decrease in maternal body weight gain in the rabbits, there were no significant effects of ondansetron on the maternal animals or the development of the offspring. At doses of 15 mg/kg/day in rats and 30 mg/kg/day in rabbits, the maternal exposure margin was approximately 6 and 24 times the maximum recommended human oral dose of 24 mg/day, respectively, based on BSA.

In a pre- and postnatal developmental toxicity study, pregnant rats received oral doses of ondansetron up to 15 mg/kg/day from Day 17 of pregnancy to litter Day 21. With the exception of a slight reduction in maternal body weight gain, there were no effects upon the pregnant rats and the pre- and postnatal development of their offspring, including reproductive performance of the mated F1 generation. At a dose of 15 mg/kg/day in rats, the maternal exposure margin was approximately 6 times the maximum recommended human oral dose of 24 mg/day, based on BSA.

8.2 Lactation

Risk Summary

It is not known whether ondansetron is present in human milk. There are no data on the effects of ondansetron on the breastfed infant or the effects on milk production. However, it has been demonstrated that ondansetron is present in the milk of rats. When a drug is present in animal milk, it is likely that the drug will be present in human milk.

The developmental and health benefits of breastfeeding should be considered along with the mother’s clinical need for ondansetron and any potential adverse effects on the breastfed infant from ondansetron or from the underlying maternal condition.

8.4 Pediatric Use

The safety and effectiveness of orally administered ondansetron have been established in pediatric patients 4 years and older for the prevention of nausea and vomiting associated with moderately emetogenic cancer chemotherapy. Use of ondansetron in these age-groups is supported by evidence from adequate and well-controlled studies of ondansetron in adults with additional data from 3 open-label, uncontrolled, non-US trials in 182 pediatric patients aged 4 to 18 years with cancer who were given a variety of cisplatin or noncisplatin regimens [see Dosage and Administration (2.2), Clinical Studies (14.1)] .

Additional information on the use of ondansetron in pediatric patients may be found in ondansetron injection prescribing information.

The safety and effectiveness of orally administered ondansetron have not been established in pediatric patients for:

- prevention of nausea and vomiting associated with highly emetogenic cancer chemotherapy
- prevention of nausea and vomiting associated with radiotherapy
- prevention of postoperative nausea and/or vomiting

8.5 Geriatric Use

Of the total number of subjects enrolled in cancer chemotherapy-induced and postoperative nausea and vomiting in US- and foreign-controlled clinical trials, for which there were subgroup analyses, 938 (19%) were aged 65 years and older.

No overall differences in safety or effectiveness were observed between subjects 65 years of age and older and younger subjects. A reduction in clearance and increase in elimination half-life were seen in patients older than 75 years compared with younger subjects [see Clinical Pharmacology (12.3)] . There were an insufficient number of patients older than 75 years of age and older in the clinical trials to permit safety or efficacy conclusions in this age group. Other reported clinical experience has not identified differences in responses between the elderly and younger patients, but greater sensitivity of some older individuals cannot be ruled out. No dosage adjustment is needed in elderly patients.

8.6 Hepatic Impairment

No dosage adjustment is needed in patients with mild or moderate hepatic impairment.

In patients with severe hepatic impairment, clearance is reduced and the apparent volume of distribution is increased, resulting in a significant increase in the half-life of ondansetron. Therefore, do not exceed a total daily dose of 8 mg in patients with severe hepatic impairment (Child-Pugh score of 10 or greater) [see Dosage and Administration (2.2), Clinical Pharmacology (12.3)] .

8.7 Renal Impairment

No dosage adjustment is recommended for patients with any degree of renal impairment (mild, moderate, or severe). There is no experience beyond first-day administration of ondansetron [see Clinical Pharmacology (12.3)] .

9 DRUG ABUSE AND DEPENDENCE

Animal studies have shown that ondansetron is not discriminated as a benzodiazepine nor does it substitute for benzodiazepines in direct addiction studies.

10 OVERDOSAGE

There is no specific antidote for ondansetron overdose. Patients should be managed with appropriate supportive therapy.

In addition to the adverse reactions listed above, the following adverse reactions have been described in the setting of ondansetron overdose: “Sudden blindness” (amaurosis) of 2 to 3 minutes’ duration plus severe constipation occurred in one patient that was administered 72 mg of ondansetron intravenously as a single dose. Hypotension (and faintness) occurred in a patient that took 48 mg of ondansetron tablets. Following infusion of 32 mg over only a 4-minute period, a vasovagal episode with transient second‑degree heart block was observed. In all instances, the adverse reactions resolved completely.

Pediatric cases consistent with serotonin syndrome have been reported after inadvertent oral overdoses of ondansetron (exceeding estimated ingestion of 5 mg per kg) in young children. Reported symptoms included somnolence, agitation, tachycardia, tachypnea, hypertension, flushing, mydriasis, diaphoresis, myoclonic movements, horizontal nystagmus, hyperreflexia, and seizure. Patients required supportive care, including intubation in some cases, with complete recovery without sequelae within 1 to 2 days.

11 DESCRIPTION

The active ingredient in Ondansetron Tablets, USP is ondansetron hydrochloride, USP as the dihydrate, the racemic form of ondansetron and a selective blocking agent of the serotonin 5-HT3 receptor type. Chemically it is (±) 1, 2, 3, 9-tetrahydro-9-methyl-3-[(2-methyl-1H-imidazol-1-yl)methyl]-4H-carbazol-4-one, monohydrochloride, dihydrate. It has the following structural formula:

The empirical formula is C18H19N3O•HCl•2H2O, representing a molecular weight of 365.85 g/mol.

Ondansetron hydrochloride, USP (dihydrate) is a white to off-white powder that is sparingly soluble in water and in alcohol; soluble in methanol, slightly soluble in isopropyl alcohol, and in dichloromethane; very slightly soluble in acetone, in chloroform and in ethyl acetate.

The active ingredient in Ondansetron Orally Disintegrating Tablets, USP is ondansetron base, the racemic form of ondansetron, and a selective blocking agent of the serotonin 5-HT3 receptor type. Chemically it is (±) 1, 2, 3, 9-tetrahydro-9-methyl-3-[(2-methyl-1H-imidazol-1-yl)methyl]-4H-carbazol-4-one. It has the following structural formula:

The empirical formula is C18H19N3O representing a molecular weight of 293.4 g/mol.

Each 4-mg Ondansetron Tablet, USP for oral administration contains ondansetron hydrochloride, USP (dihydrate) equivalent to 4 mg of ondansetron. Each 8-mg Ondansetron Tablet, USP for oral administration contains ondansetron hydrochloride, USP (dihydrate) equivalent to 8 mg of ondansetron. Each tablet also contains the inactive ingredients colloidal silicon dioxide, hypromellose, iron oxide yellow (8 mg tablet only), lactose monohydrate, magnesium stearate, microcrystalline cellulose, pregelatinized starch, titanium dioxide and triacetin.

Each 4-mg Ondansetron Orally Disintegrating Tablet, USP for oral administration contains 4 mg ondansetron base. Each 8-mg Ondansetron Orally Disintegrating Tablet, USP for oral administration contains 8 mg ondansetron base. Each Ondansetron Orally Disintegrating Tablet, USP also contains the inactive ingredients aspartame, colloidal silicon dioxide, crospovidone, magnesium stearate, mannitol, sodium stearyl fumarate and strawberry flavor. Ondansetron Orally Disintegrating Tablets, USP are an orally administered formulation of ondansetron which rapidly disintegrates on the tongue and does not require water to aid dissolution or swallowing. This product disintegrates in approximately 60 seconds.

Ondansetron Orally Disintegrating Tablets, USP meet USP Disintegration Test 2.

12 CLINICAL PHARMACOLOGY

12.1 Mechanism of Action

Ondansetron is a selective 5‑HT3 receptor antagonist. While its mechanism of action has not been fully characterized, ondansetron is not a dopamine‑receptor antagonist. Serotonin receptors of the 5‑HT3 type are present both peripherally on vagal nerve terminals and centrally in the chemoreceptor trigger zone of the area postrema. It is not certain whether ondansetron’s antiemetic action is mediated centrally, peripherally, or in both sites. However, cytotoxic chemotherapy appears to be associated with release of serotonin from the enterochromaffin cells of the small intestine. In humans, urinary 5‑hydroxyindoleacetic acid (5‑HIAA) excretion increases after cisplatin administration in parallel with the onset of emesis. The released serotonin may stimulate the vagal afferents through the 5‑HT3 receptors and initiate the vomiting reflex.

12.2 Pharmacodynamics

In healthy subjects, single intravenous doses of 0.15 mg/kg of ondansetron had no effect on esophageal motility, gastric motility, lower esophageal sphincter pressure, or small intestinal transit time. Multiday administration of ondansetron has been shown to slow colonic transit in healthy subjects. Ondansetron has no effect on plasma-prolactin concentrations.

Cardiac Electrophysiology

QTc interval prolongation was studied in a double-blind, single-intravenous dose, placebo- and positive-controlled, crossover trial in 58 healthy subjects. The maximum mean (95% upper confidence bound) difference in QTcF from placebo after baseline correction was 19.5 (21.8) milliseconds and 5.6 (7.4) milliseconds after 15-minute intravenous infusions of 32 mg and 8 mg of ondansetron injection, respectively. A significant exposure-response relationship was identified between ondansetron concentration and ΔΔQTcF. Using the established exposure-response relationship, 24 mg infused intravenously over 15 minutes had a mean predicted (95% upper prediction interval) ΔΔQTcF of 14 (16.3) milliseconds. In contrast, 16 mg infused intravenously over 15 minutes using the same model had a mean predicted (95% upper prediction interval) ΔΔQTcF of 9.1 (11.2) milliseconds. In this study, the 8-mg dose infused over 15 minutes did not prolong the QT interval to any clinically relevant extent.

12.3 Pharmacokinetics

Absorption

Ondansetron is absorbed from the gastrointestinal tract and undergoes some first‑pass metabolism. Mean bioavailability in healthy subjects, following administration of a single 8‑mg tablet, is approximately 56%.

Ondansetron systemic exposure does not increase proportionately to dose. The area under curve (AUC) from a 16‑mg tablet was 24% greater than predicted from an 8‑mg tablet dose. This may reflect some reduction of first‑pass metabolism at higher oral doses.

Food Effects: Bioavailability is also slightly enhanced by the presence of food.

Distribution

Plasma protein binding of ondansetron as measured in vitro was 70% to 76% over the concentration range of 10 to 500 ng/mL. Circulating drug also distributes into erythrocytes.

Elimination

Metabolism and Excretion: Ondansetron is extensively metabolized in humans, with approximately 5% of a radiolabeled dose recovered as the parent compound from the urine. The metabolites are observed in the urine. The primary metabolic pathway is hydroxylation on the indole ring followed by subsequent glucuronide or sulfate conjugation.

In vitro metabolism studies have shown that ondansetron is a substrate for human hepatic cytochrome P‑450 enzymes, including CYP1A2, CYP2D6, and CYP3A4. In terms of overall ondansetron turnover, CYP3A4 played the predominant role. Because of the multiplicity of metabolic enzymes capable of metabolizing ondansetron, it is likely that inhibition or loss of one enzyme (e.g., CYP2D6 genetic deficiency) will be compensated by others and may result in little change in overall rates of ondansetron elimination.

Although some nonconjugated metabolites have pharmacologic activity, these are not found in plasma at concentrations likely to significantly contribute to the biological activity of ondansetron.

Specific Populations

Age: Geriatric Population: A reduction in clearance and increase in elimination half‑life are seen in patients older than 75 years compared to younger subjects [see Use in Specific Populations (8.5)] .

Sex: Gender differences were shown in the disposition of ondansetron given as a single dose. The extent and rate of absorption are greater in women than men. Slower clearance in women, a smaller apparent volume of distribution (adjusted for weight), and higher absolute bioavailability resulted in higher plasma ondansetron concentrations. These higher plasma concentrations may in part be explained by differences in body weight between men and women. It is not known whether these sex-related differences were clinically important. More detailed pharmacokinetic information is contained in Tables 5 and 6.

Table 5: Pharmacokinetics in Male and Female Healthy Subjects After a Single Dose of a Ondansetron 8‑mg Tablet
Age-group; (years); Sex (M/F) | Mean; Weight; (kg) | N | Peak Plasma; Concentration; (ng/mL) | Time of; Peak Plasma; Concentration; (h) | Mean; Elimination; Half-life; (h) | Systemic; Plasma; Clearance; L/h/kg | Absolute; Bioavailability
1. 18 to 40 M | 69 | 6 | 26.2 | 2 | 3.1 | 0.403 | 0.483
1. F | 62.7 | 5 | 42.7 | 1.7 | 3.5 | 0.354 | 0.663
1. 61 to 74 M | 77.5 | 6 | 24.1 | 2.1 | 4.1 | 0.384 | 0.585
1. F | 60.2 | 6 | 52.4 | 1.9 | 4.9 | 0.255 | 0.643
1. ≥75 M | 78 | 5 | 37 | 2.2 | 4.5 | 0.277 | 0.619
1. F | 67.6 | 6 | 46.1 | 2.1 | 6.2 | 0.249 | 0.747

Table 6: Pharmacokinetics in Male and Female Healthy Subjects After a Single Dose of a Ondansetron 24-mg Tablet
Age-group; (years); Sex (M/F) | Mean; Weight; (kg) | N | Peak Plasma; Concentration; (ng/mL) | Time of; Peak Plasma; Concentration; (h) | Mean; Elimination; Half-life; (h)
- 18 to 43 M | 84.1 | 8 | 125.8 | 1.9 | 4.7
1. F | 71.8 | 8 | 194.4 | 1.6 | 5.8

Renal Impairment: Renal impairment is not expected to significantly influence the total clearance of ondansetron as renal clearance represents only 5% of the overall clearance. However, the mean plasma clearance of ondansetron was reduced by about 50% in patients with severe renal impairment (creatinine clearance less than 30 mL/min). The reduction in clearance was variable and not consistent with an increase in half‑life [see Use in Specific Populations (8.7)] .

Hepatic Impairment: In patients with mild-to-moderate hepatic impairment, clearance is reduced 2‑fold and mean half‑life is increased to 11.6 hours compared with 5.7 hours in healthy subjects. In patients with severe hepatic impairment (Child‑Pugh score of 10 or greater), clearance is reduced 2-fold to 3-fold and apparent volume of distribution is increased with a resultant increase in half‑life to 20 hours [see Dosage and Administration (2.2), Use in Specific Populations (8.6)] .

Drug Interaction Studies

CYP 3A4 Inducers: Ondansetron elimination may be affected by cytochrome P-450 inducers. In a pharmacokinetic trial of 16 epileptic patients maintained chronically on CYP3A4 inducers, carbamazepine, or phenytoin, a reduction in AUC, Cmax, and t½ of ondansetron was observed. This resulted in a significant increase in the clearance of ondansetron. However, this increase is not thought to be clinically relevant [see Drug Interactions (7.2)] .

Chemotherapeutic Agents: Carmustine, etoposide, and cisplatin do not affect the pharmacokinetics of ondansetron [see Drug Interactions (7.4)] .

Antacids: Concomitant administration of antacids does not alter the absorption of ondansetron.

13 NONCLINICAL TOXICOLOGY

13.1 Carcinogenesis, Mutagenesis, Impairment of Fertility

Carcinogenic effects were not seen in 2-year studies in rats and mice with oral ondansetron doses up to 10 mg/kg per day and 30 mg/kg per day, respectively (approximately 4 and 6 times the maximum recommended human oral dose of 24 mg per day, based on BSA).

Ondansetron was not mutagenic in standard tests for mutagenicity.

Oral administration of ondansetron up to 15 mg/kg per day (approximately 6 times the maximum recommended human oral dose of 24 mg per day, based on BSA) did not affect fertility or general reproductive performance of male and female rats.

14 CLINICAL STUDIES

14.1 Prevention of Chemotherapy-Induced Nausea and Vomiting

Highly Emetogenic Chemotherapy

In 2 randomized, double-blind, monotherapy trials, a single 24-mg oral dose of ondansetron was superior to a relevant historical placebo control in the prevention of nausea and vomiting associated with highly emetogenic cancer chemotherapy, including cisplatin greater than or equal to 50 mg/m^2. Steroid administration was excluded from these clinical trials. More than 90% of patients receiving a cisplatin dose greater than or equal to 50 mg/m^2 in the historical-placebo comparator, experienced vomiting in the absence of antiemetic therapy.

The first trial compared oral doses of ondansetron 24 mg as a single dose, 8 mg every 8 hours for 2 doses, and 32 mg as a single dose in 357 adult cancer patients receiving chemotherapy regimens containing cisplatin greater than or equal to 50 mg/m^2. The first or single dose was administered 30 minutes prior to chemotherapy. A total of 66% of patients in the ondansetron 24-mg once-a-day group, 55% in the ondansetron 8‑mg twice-a-day group, and 55% in the ondansetron 32‑mg once-a-day group, completed the 24-hour trial period with 0 emetic episodes and no rescue antiemetic medications, the primary endpoint of efficacy. Each of the 3 treatment groups was shown to be statistically significantly superior to a historical placebo control.

In the same trial, 56% of patients receiving a single 24-mg oral dose of ondansetron experienced no nausea during the 24-hour trial period, compared with 36% of patients in the oral ondansetron 8‑mg twice-a-day group (P = 0.001) and 50% in the oral ondansetron 32-mg once-a-day group. Dosage regimens of ondansetron 8 mg twice daily and 32 mg once daily are not recommended for the prevention of nausea and vomiting associated with highly emetogenic chemotherapy [see Dosage and Administration (2.1)] .

In a second trial, efficacy of a single 24-mg oral dose of ondansetron for the prevention of nausea and vomiting associated with highly emetogenic cancer chemotherapy, including cisplatin greater than or equal to 50 mg/m^2, was confirmed.

Moderately Emetogenic Chemotherapy

A randomized, placebo-controlled, double‑blind trial was conducted in the US in 67 patients receiving a cyclophosphamide‑based chemotherapy regimen containing doxorubicin. The first 8-mg dose of ondansetron was administered 30 minutes before the start of chemotherapy, with a subsequent dose 8 hours after the first dose, followed by 8 mg of ondansetron twice a day for 2 days after the completion of chemotherapy.

Ondansetron was significantly more effective than placebo in preventing vomiting. Treatment response was based on the total number of emetic episodes over the 3-day trial period. The results of this trial are summarized in Table 7.

Table 7: Emetic Episodes - Treatment Response in Patients Receiving Moderately Emetogenic Chemotherapy (Cyclophosphamide-based Regimen Containing Doxorubicin)
 | Ondansetron; (n = 33) | Placebo; (n = 34) | P-value
Treatment response
0 Emetic episodes | 20 (61%) | 2 (6%) | <0.001
1 to 2 Emetic episodes | 6 (18%) | 8 (24%)
More than 2 emetic episodes/withdrawn | 7 (21%) | 24 (71%) | <0.001
Median number of emetic episodes | 0 | Undefineda
Median time to first emetic episode (hours) | Undefinedb | 6.5

- a Median undefined since at least 50% of the patients were withdrawn or had more than 2 emetic episodes.
- b Median undefined since at least 50% of patients did not have any emetic episodes.

In a double‑blind, US trial in 336 patients receiving a cyclophosphamide‑based chemotherapy regimen containing either methotrexate or doxorubicin, ondansetron 8 mg administered twice a day, was as effective as ondansetron 8 mg administered 3 times a day in preventing nausea and vomiting. Ondansetron 8 mg three times daily is not a recommended regimen for the treatment of moderately emetogenic chemotherapy [see Dosage and Administration (2.1)] .

Treatment response was based on the total number of emetic episodes over the 3-day trial period. See Table 8 for the details of the dosage regimens studied and results of this trial.

Table 8: Emetic Episodes - Treatment Response After Ondansetron Tablets Administered Twice a Day and Three Times a Day
 | Ondansetron Tablets
 | 8 mg Twice Dailya; (n = 165) | 8 mg Three Times a Dayb; (n = 171)
Treatment response
0 Emetic episodes | 101 (61%) | 99 (58%)
1 to 2 Emetic episodes | 16 (10%) | 17 (10%)
More than 2 emetic episodes/withdrawn | 48 (29%) | 55 (32%)
Median number of emetic episodes | 0 | 0
Median time to first emetic episode (h) | Undefinedc | Undefinedc
Median nausea scores (0 to 100)d | 6 | 6

- a The first 8-mg dose was administered 30 minutes before the start of emetogenic chemotherapy, with a subsequent 8-mg dose 8 hours after the first dose, followed by 8 mg administered twice a day for 2 days after the completion of chemotherapy.
- b The first 8-mg dose was administered 30 minutes before the start of emetogenic chemotherapy, with subsequent 8-mg doses at 4 hours and 8 hours after the first dose, followed by 8 mg administered 3 times a day for 2 days after the completion of chemotherapy.
- c Median undefined since at least 50% of patients did not have any emetic episodes.
- d Visual analog scale assessment: 0 = no nausea, 100 = nausea as bad as it can be.

Re‑ treatment

In single-arm trials, 148 patients receiving cyclophosphamide‑based chemotherapy were re‑treated with ondansetron 8 mg three times daily during subsequent chemotherapy for a total of 396 re‑treatment courses. No emetic episodes occurred in 314 (79%) of the re-treatment courses, and only 1 to 2 emetic episodes occurred in 43 (11%) of the re‑treatment courses.

Pediatric Trials

Three open‑label, single-arm, non-US trials have been performed with 182 pediatric patients aged 4 to 18 years with cancer who were given a variety of cisplatin or noncisplatin regimens. The initial dose of ondansetron injection ranged from 0.04 to 0.87 mg per kg (total dose of 2.16 mg to 12 mg) followed by the administration of oral doses of ondansetron ranging from 4 to 24 mg daily for 3 days. In these trials, 58% of the 170 evaluable patients had a complete response (no emetic episodes) on Day 1. In 2 trials, the response rates to ondansetron 4 mg three times a day in patients younger than 12 years was similar to ondansetron 8 mg three times daily in patients 12 to 18 years. Prevention of emesis in these pediatric patients was essentially the same as for adults.

14.2 Radiation-Induced Nausea and Vomiting

Total Body Irradiation

In a randomized, placebo-controlled, double‑blind trial in 20 patients, 8 mg of ondansetron administered 1.5 hours before each fraction of radiotherapy for 4 days was significantly more effective than placebo in preventing vomiting induced by total body irradiation. Total body irradiation consisted of 11 fractions (120 cGy per fraction) over 4 days for a total of 1,320 cGy. Patients received 3 fractions for 3 days, then 2 fractions on Day 4.

Single High‑ Dose Fraction Radiotherapy

In an active-controlled, double‑blind trial in 105 patients receiving single high‑dose radiotherapy (800 to 1,000 cGy) over an anterior or posterior field size of greater than or equal to 80 cm^2 to the abdomen, ondansetron was significantly more effective than metoclopramide with respect to complete control of emesis (0 emetic episodes). Patients received the first dose of ondansetron (8 mg) or metoclopramide (10 mg) 1 to 2 hours before radiotherapy. If radiotherapy was given in the morning, 8 mg of ondansetron or 10 mg of metoclopramide was administered in the late afternoon and repeated again before bedtime. If radiotherapy was given in the afternoon, patients took 8 mg of ondansetron or 10 mg of metoclopramide only once before bedtime. Patients continued the doses of oral medication three times daily for 3 days.

Daily Fractionated Radiotherapy

In an active-controlled, double‑blind trial in 135 patients receiving a 1- to 4- week course of fractionated radiotherapy (180 cGy doses) over a field size of greater than or equal to 100 cm^2 to the abdomen, ondansetron was significantly more effective than prochlorperazine with respect to complete control of emesis (0 emetic episodes). Patients received the first dose of ondansetron (8 mg) or prochlorperazine (10 mg) 1 to 2 hours before the first daily radiotherapy fraction, with subsequent 8-mg doses approximately every 8 hours on each day of radiotherapy.

14.3 Postoperative Nausea and/ or Vomiting

In 2 placebo-controlled, double-blind trials (one conducted in the US and the other outside the US) in 865 females undergoing inpatient surgical procedures, ondansetron 16 mg as a single dose or placebo was administered one hour before the induction of general balanced anesthesia (barbiturate, opioid, nitrous oxide, neuromuscular blockade, and supplemental isoflurane or enflurane), ondansetron tablets was significantly more effective than placebo in preventing postoperative nausea and vomiting.

No trials have been performed in males.

16 HOW SUPPLIED/STORAGE AND HANDLING

Ondansetron Orally Disintegrating Tablets, USP

4 mg (as 4 mg ondansetron base) are white, circular, flat faced, uncoated tablets with ‘G’ engraved on one side and ‘4’ on the other side in:

NDC: 70518-3512-00

NDC: 70518-3512-01

NDC: 70518-3512-02

NDC: 70518-3512-03

NDC: 70518-3512-04
NDC: 70518-3512-05

NDC: 70518-3512-06

NDC: 70518-3512-07

NDC: 70518-3512-08

PACKAGING: 30 in 1 BOX, UNIT DOSE

PACKAGING: 6 in 1 BOX, UNIT DOSE

PACKAGING: 10 in 1 BOX, UNIT DOSE

PACKAGING: 20 in 1 BOX, UNIT DOSE

PACKAGING: 12 in 1 BOX, UNIT DOSE
PACKAGING: 9 in 1 BOX, UNIT DOSE

PACKAGING: 21 in 1 BOX, UNIT DOSE

PACKAGING: 15 in 1 BOX, UNIT DOSE

PACKAGING: 3 in 1 BOX, UNIT DOSE

Store at 20°C to 25°C (68°F to 77°F) [see USP Controlled Room Temperature].

Repackaged and Distributed By:

Remedy Repack, Inc.

625 Kolter Dr. Suite #4 Indiana, PA 1-724-465-8762

17 PATIENT COUNSELING INFORMATION

Hypersensitivity Reactions

Inform patients that ondansetron may cause hypersensitivity reactions, some as severe as anaphylaxis and bronchospasm. Instruct patients to immediately report any signs and symptoms of hypersensitivity reactions, including fever, chills, rash, or breathing problems to their healthcare provider [ see Warnings and Precautions (5.1) ].

QT Prolongation

Inform patients that ondansetron may cause serious cardiac arrhythmias, such as QT prolongation. Instruct patients to tell their healthcare provider right away if they perceive a change in their heart rate, if they feel lightheaded, or if they have a syncopal episode [ see Warnings and Precautions (5.2) ].

Drug Interactions

- Instruct the patient to report the use of all medications, especially apomorphine, to their healthcare provider. Concomitant use of apomorphine and ondansetron may cause a significant drop in blood pressure and loss of consciousness.
- Advise patients of the possibility of serotonin syndrome with concomitant use of ondansetron and another serotonergic agent, such as medications to treat depression and migraines. Advise patients to seek immediate medical attention if the following symptoms occur: changes in mental status, autonomic instability, neuromuscular symptoms with or without gastrointestinal symptoms [ see Warnings and Precautions (5.3) ].

Myocardial Ischemia

Inform patients that ondansetron may cause myocardial ischemia. Advise patients to seek immediate medical help if any symptoms suggestive of a myocardial ischemia occur, such as sudden chest pain or chest tightness [see Warnings and Precautions (5.4)] .

Masking of Progressive Ileus and Gastric Distension

Inform patients following abdominal surgery or those with chemotherapy‑induced nausea and vomiting that ondansetron may mask signs and symptoms of bowel obstruction. Instruct patients to immediately report any signs or symptoms consistent with a potential bowel obstruction to their healthcare provider [ see Warnings and Precautions (5.5) ].

Administration of Ondansetron Orally Disintegrating Tablets

Instruct patients not to remove ondansetron orally disintegrating tablets from the blister until just prior to dosing.

- Do not attempt to push ondansetron orally disintegrating tablets through the foil backing.
- With dry hands, peel back the foil backing of 1 blister and gently remove the tablet.
- Immediately place the ondansetron orally disintegrating tablet on top of the tongue where it will dissolve in seconds, then swallow with saliva.
- Administration with liquid is not necessary.
- Peelable illustrated stickers are affixed to the product carton that can be provided with the prescription to ensure proper use and handling of the product.

Repackaged By / Distributed By: RemedyRepack Inc.

625 Kolter Drive, Indiana, PA 15701

(724) 465-8762

RECENT MAJOR CHANGES

Warnings and Precautions, Myocardial Ischemia (5.4) 10/2021

PRINCIPAL DISPLAY PANEL

DRUG: Ondansetron

GENERIC: Ondansetron

DOSAGE: TABLET, ORALLY DISINTEGRATING

ADMINSTRATION: ORAL

NDC: 70518-3512-0

NDC: 70518-3512-1

NDC: 70518-3512-2

NDC: 70518-3512-3

NDC: 70518-3512-4

NDC: 70518-3512-5

NDC: 70518-3512-6

NDC: 70518-3512-7

NDC: 70518-3512-8

COLOR: white

FLAVOR: STRAWBERRY

SHAPE: ROUND

SCORE: No score

SIZE: 7 mm

IMPRINT: G;4

PACKAGING: 30 in 1 BOX, UNIT-DOSE

PACKAGING: 6 in 1 BOX, UNIT-DOSE

PACKAGING: 10 in 1 BOX, UNIT-DOSE

PACKAGING: 20 in 1 BOX, UNIT-DOSE

PACKAGING: 12 in 1 BOX, UNIT DOSE
PACKAGING: 9 in 1 BOX, UNIT DOSE

PACKAGING: 21 in 1 BOX, UNIT DOSE

PACKAGING: 15 in 1 BOX, UNIT DOSE

PACKAGING: 3 in 1 BOX, UNIT DOSE

ACTIVE INGREDIENT(S):

- ONDANSETRON 4mg in 1

INACTIVE INGREDIENT(S):

- ASPARTAME
- SILICON DIOXIDE
- CROSPOVIDONE (120 .MU.M)
- MAGNESIUM STEARATE
- MANNITOL
- SODIUM STEARYL FUMARATE